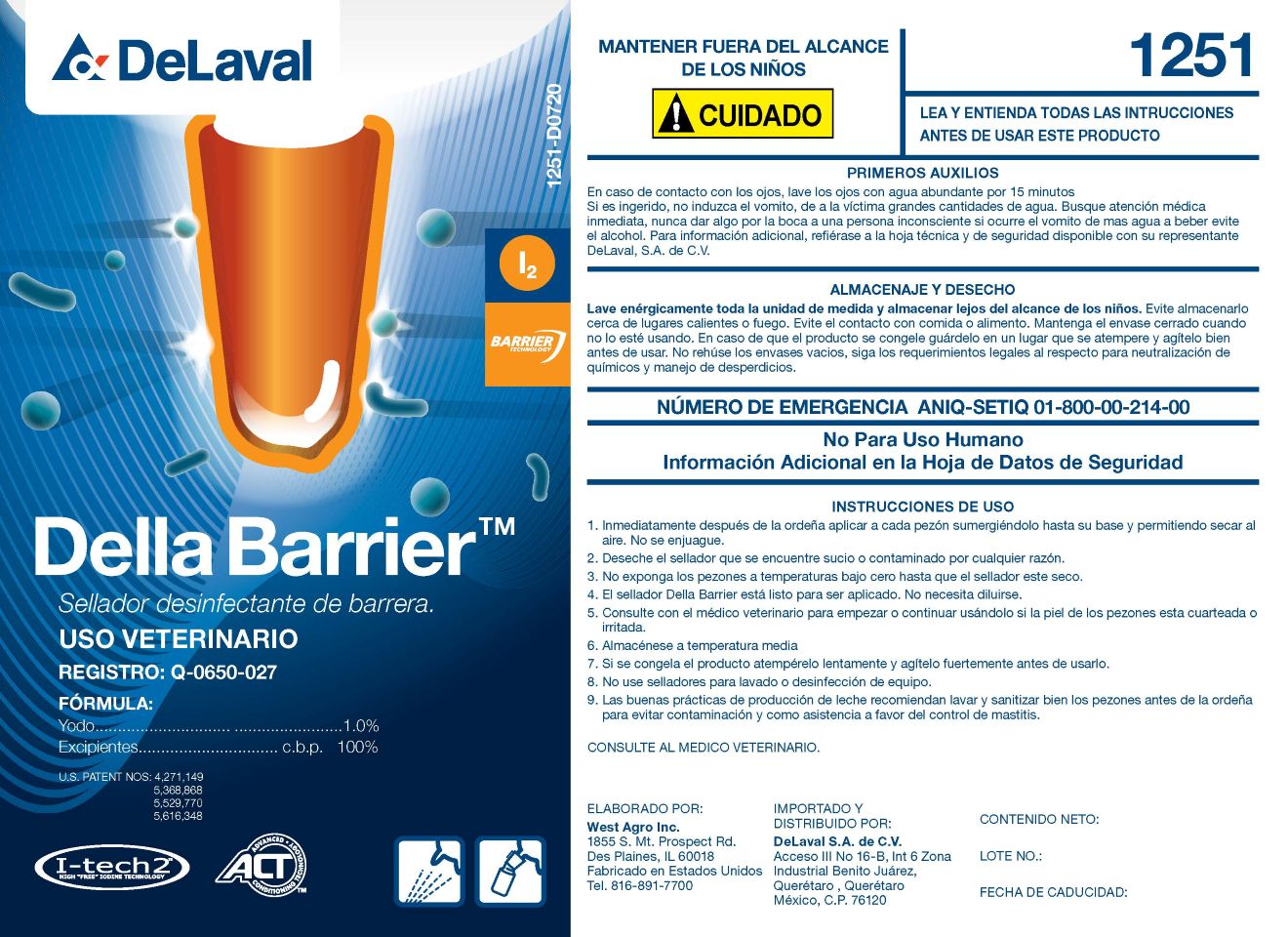 DRUG LABEL: Della Barrier
NDC: 55756-251 | Form: SOLUTION
Manufacturer: DeLaval
Category: animal | Type: OTC ANIMAL DRUG LABEL
Date: 20251220

ACTIVE INGREDIENTS: IODINE 10 g/1 L

DeLaval Della Barrier

Disinfectant barrier sealant

Registration: Q-0650-027

ACTIVE INGREDIENTS:
Iodine .................................................... 1.00%

Excipients................sufficient quantity for....100%

US Patent Nos.: 4,271.149, 5,368,868, 5,529,770, 5,616,348

KEEP OUT OF REACH OF CHILDREN
Warning

READ AND UNDERSTAND ALL INSTRUCTIONS BEFORE USING THIS PRODUCT

FIRST AID

Thoruoughly wash the entire measuring unit and store out of reach of children.

Avoid storing it near heat or fire. Avoid contact with food. Keep the container closed when not in use

If the product freezes, store it in a thawed place and shake well before use.

Do not reuse emoty containers: Follow legal requirements for chemiccal neutralization and waste disposal.

Contact with product can cause irritation to eyes. Avoid contact with eyes.

ANIQ-SETIQ Emergency Number 01-800-00-214-00

Not for Human Use. Additional information is the Safety Data Sheet.

INDICATIONS AND USAGE

Instructions for Use

1. Immediately after milking, apply to each teat, immersing it to its base and allowing it to air dry. Do not rinse.

2. Discard any teat sealant that is soiled or contaminated for any reason.

3. Do not expose teats to freezing temperatures until the sealant is dry.

4. Della Barrier Teat Sealant is ready to use. It does not need to be diluted.

5. Consult your veterinarian before starting or continuing to use if the teat skin is cracked or irritated.

6. Store at room temperature.

7. If the product freezes, that it slowly and shake vigorously before use.

8. Do not use teat sealants for wahsing or disinfecting equipment.

9 Good dairy production pratices recommend washing and sanitizing teats thoroughly before milking to prevent contamination

and as an aid in mastitis control.

Consult Your Veterinarian.

Prepared By:

West Agro, Inc.
1855 S Mt. Prospect Rd.

Des Plaines, IL 60018

Made in the USA.

Tel. 816-891-7700

Imported and Distributed By:

DeLaval S.A. de C.V.

Acceso III No 16-B, Int 6 Zona

Industrial Benito Juarez

Queretaro, Queretaro

Mexico, C.P. 76120

NET CONTENTS:

LOT NO.:

EXP. DATE: